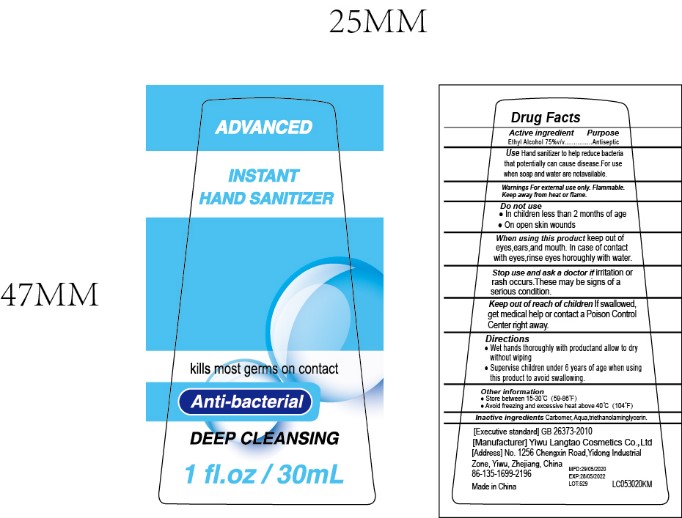 DRUG LABEL: Hand Sanitizer
NDC: 77207-136 | Form: GEL
Manufacturer: Yiwu Langtao Cosmetics Co., Ltd
Category: otc | Type: HUMAN OTC DRUG LABEL
Date: 20210816

ACTIVE INGREDIENTS: ALCOHOL 22.5 mL/30 mL
INACTIVE INGREDIENTS: TROLAMINE 0.102 mL/30 mL; GLYCERIN 0.18 mL/30 mL; CARBOMER 980 0.15 mL/30 mL; WATER 7.068 mL/30 mL

Active Ingredient(s)

Alcohol 75% v/v. Purpose: Antiseptic

Purpose

Antiseptic, Hand Sanitizer

Use

- To decrease bacteria on the skin
- Recommended for repeated use

Warnings

For external use only-hands. Flammable. Keep away from heat or flame. Not recommended for infants.

Do not use

- Children under 4 year of age
- on open skin wounds

When using this product keep out of eyes, ears, and mouth. In case of contact with eyes, rinse eyes thoroughly with water.
Stop use and ask a doctor if irritation or rash occurs. These may be signs of a serious condition.
Keep out of reach of children. If swallowed, get medical help or contact a Poison Control Center right away.

Stop use and ask a doctor if skin irritation develops.

Keep out of reach of children. If swallowed, get medical help or contact a Poison Control Center right away.

Directions

- Wet hands thoroughly with product and allow to dry
- Store in cool dry place

Inactive ingredients

carbomer, sterile distilled water, triethanolamine.

Package Label - Principal Display Panel

30 mL NDC: 77207-136-1